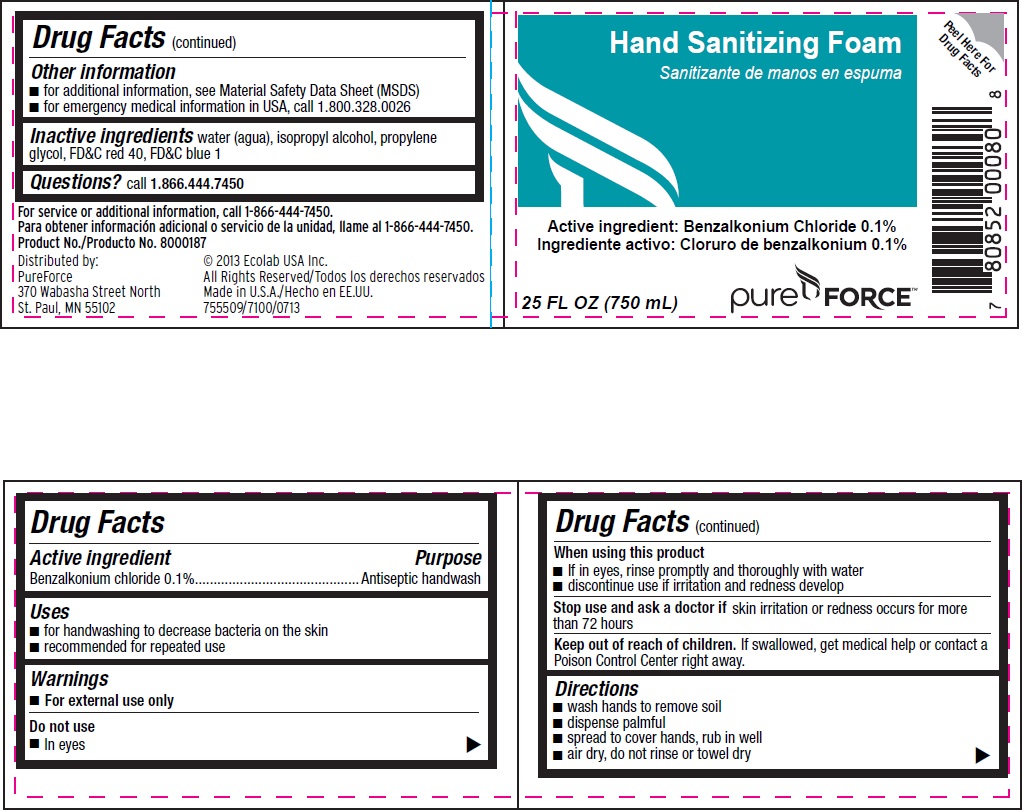 DRUG LABEL: Pure Force
NDC: 47593-504 | Form: LIQUID
Manufacturer: Ecolab Inc.
Category: otc | Type: HUMAN OTC DRUG LABEL
Date: 20240709

ACTIVE INGREDIENTS: BENZALKONIUM CHLORIDE 1 mg/1 mL
INACTIVE INGREDIENTS: WATER; ISOPROPYL ALCOHOL; PROPYLENE GLYCOL; FD&C RED NO. 40; FD&C BLUE NO. 1

Drug Facts

Active Ingredient

Benzalkonium chloride 0.1%

Purpose

Antiseptic handwash

Uses

- for handwashing to decrease bacteria on the skin
- recommended for repeated use

Warnings

- For external use only

Do not use

- In eyes

When using this product

- If in eyes, rinse promptly and thoroughly with water
- discontinue use if irritation and redness develop

Stop use and ask a doctor if skin irritation or redness occurs for more than 72 hours

Keep out of reach of children. If swallowed, get medical help or contact a Poison Control Center right away.

Directions

- wash hands to remove soil
- dispense palmful
- spread to cover hands, rub in well
- air dry, do not rinse or towel dry

Other information

- for additional information, see Material Safety Data Sheet (MSDS)
- for emergency medical information in USA, call 1.800.328.0026

INACTIVE INGREDIENT

Inactive ingredients water (aqua), isopropoyl alcohol, propylene glycol, FDC red 40, FDC blue 1

Questions? call 1.866.444.7450

Principal Display Panel with Representative Label

Hand Sanitizing Foam

Active ingredient: Benzalkonium chloride 0.1%

25 FL OZ (750 mL)

Pure Force™

Distributed by: © 2013 Ecolab USA Inc.

PureForce All Rights Reserved

370 Wabasha Street North Made in U.S.A.

St. Paul, MN 55102 755509/7100/0713